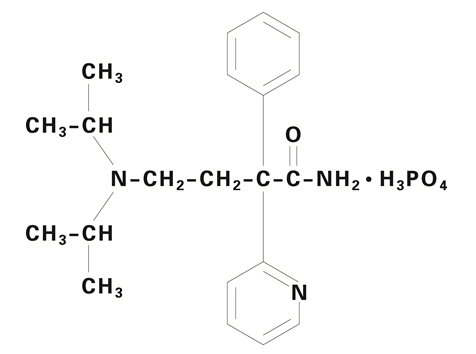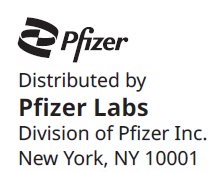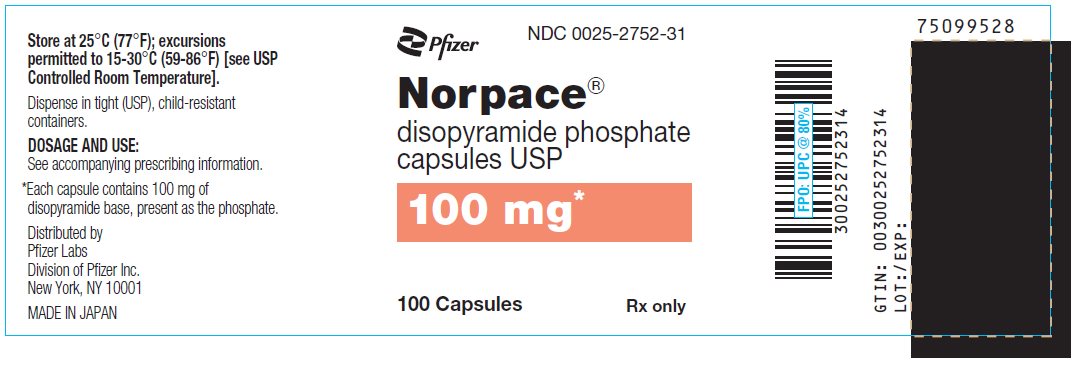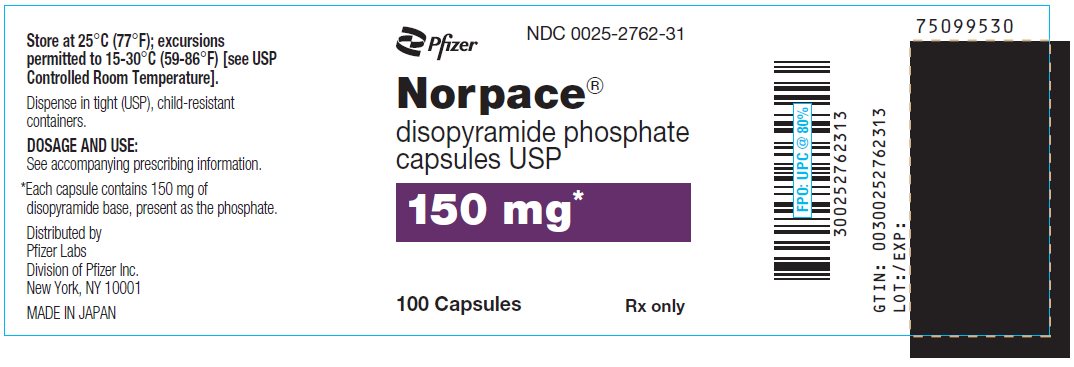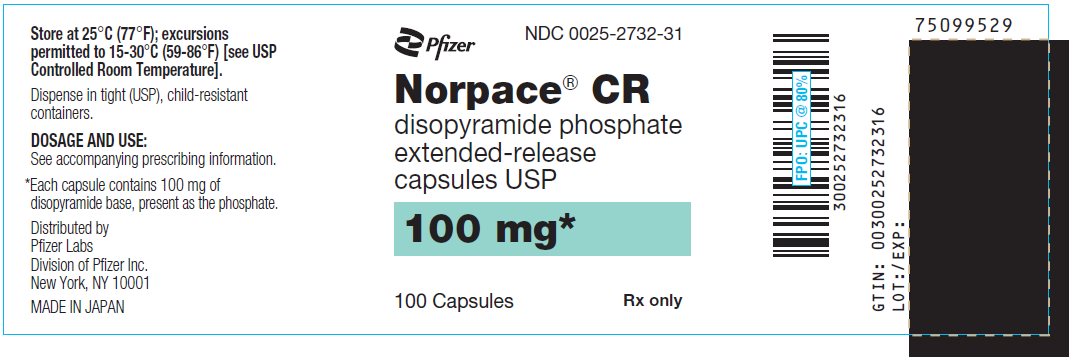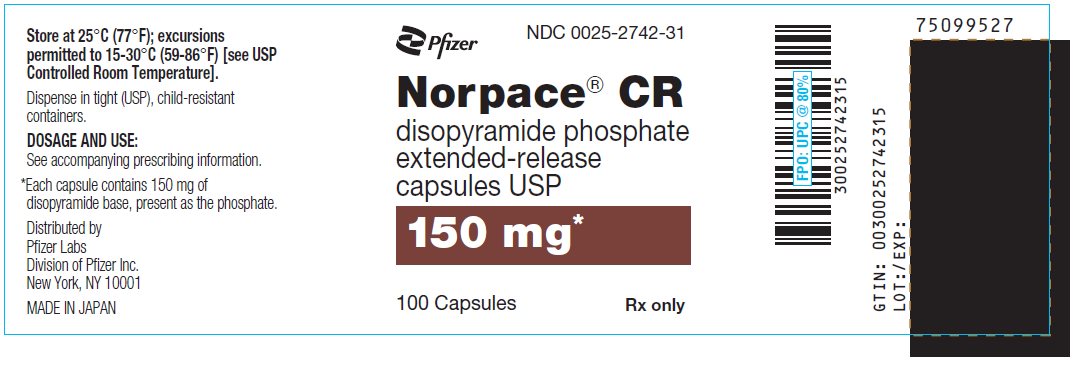 DRUG LABEL: Norpace
NDC: 0025-2752 | Form: CAPSULE, GELATIN COATED
Manufacturer: Pfizer Laboratories Div Pfizer Inc
Category: prescription | Type: HUMAN PRESCRIPTION DRUG LABEL
Date: 20250804

ACTIVE INGREDIENTS: DISOPYRAMIDE PHOSPHATE 100 mg/1 1
INACTIVE INGREDIENTS: STARCH, CORN; FD&C RED NO. 3; FD&C YELLOW NO. 6; GELATIN, UNSPECIFIED; LACTOSE, UNSPECIFIED FORM; TALC; TITANIUM DIOXIDE

Norpace®
disopyramide phosphate capsules
Norpace® CR
disopyramide phosphate extended-release capsules

DESCRIPTION

Norpace (disopyramide phosphate) is an antiarrhythmic drug available for oral administration in immediate-release and controlled-release capsules containing 100 mg or 150 mg of disopyramide base, present as the phosphate. The base content of the phosphate salt is 77.6%. The structural formula of Norpace is:

α-[2-(diisopropylamino) ethyl]-α-phenyl- 2-pyridineacetamide phosphate

Norpace is freely soluble in water, and the free base (pKa 10.4) has an aqueous solubility of 1 mg/ml. The chloroform:water partition coefficient of the base is 3.1 at pH 7.2.

Norpace is a racemic mixture of d- and l- isomers. This drug is not chemically related to other antiarrhythmic drugs.

Norpace CR (controlled-release) capsules are designed to afford a gradual and consistent release of disopyramide. Thus, for maintenance therapy, Norpace CR provides the benefit of less-frequent dosing (every 12 hours) as compared with the every-6-hour dosage schedule of immediate-release Norpace capsules.

Inactive ingredients of Norpace include corn starch, edible ink, FD&C Red No. 3, FD&C Yellow No. 6, gelatin, lactose, talc, and titanium dioxide; the 150-mg capsule also contains FD&C Blue No. 1.

Inactive ingredients of Norpace CR include corn starch, D&C Yellow No. 10, edible ink, ethylcellulose, FD&C Blue No. 1, gelatin, shellac, sucrose, talc, and titanium dioxide; the 150-mg capsule also contains FD&C Red No. 3 and FD&C Yellow No. 6.

CLINICAL PHARMACOLOGY

Mechanisms of Action

Norpace (disopyramide phosphate) is a Type 1 antiarrhythmic drug (i.e., similar to procainamide and quinidine). In animal studies Norpace decreases the rate of diastolic depolarization (phase 4) in cells with augmented automaticity, decreases the upstroke velocity (phase 0) and increases the action potential duration of normal cardiac cells, decreases the disparity in refractoriness between infarcted and adjacent normally perfused myocardium, and has no effect on alpha- or beta-adrenergic receptors.

Electrophysiology

In man, Norpace at therapeutic plasma levels shortens the sinus node recovery time, lengthens the effective refractory period of the atrium, and has a minimal effect on the effective refractory period of the AV node. Little effect has been shown on AV-nodal and His-Purkinje conduction times or QRS duration. However, prolongation of conduction in accessory pathways occurs.

Hemodynamics

At recommended oral doses, Norpace rarely produces significant alterations of blood pressure in patients without congestive heart failure (see Warnings). With intravenous Norpace, either increases in systolic/diastolic or decreases in systolic blood pressure have been reported, depending on the infusion rate and the patient population. Intravenous Norpace may cause cardiac depression with an approximate mean 10% reduction of cardiac output, which is more pronounced in patients with cardiac dysfunction.

Anticholinergic Activity

The in vitro anticholinergic activity of Norpace is approximately 0.06% that of atropine; however, the usual dose for Norpace is 150 mg every 6 hours and for Norpace CR 300 mg every 12 hours, compared to 0.4 to 0.6 mg for atropine (see Warnings and Adverse Reactions for anticholinergic side effects).

Pharmacokinetics

Following oral administration of immediate-release Norpace, disopyramide phosphate is rapidly and almost completely absorbed, and peak plasma levels are usually attained within 2 hours. The usual therapeutic plasma levels of disopyramide base are 2 to 4 mcg/ml, and at these concentrations protein binding varies from 50% to 65%. Because of concentration-dependent protein binding, it is difficult to predict the concentration of the free drug when total drug is measured.

The mean plasma half-life of disopyramide in healthy humans is 6.7 hours (range of 4 to 10 hours). In six patients with impaired renal function (creatinine clearance less than 40 ml/min), disopyramide half-life values were 8 to 18 hours.

After the oral administration of 200 mg of disopyramide to 10 cardiac patients with borderline to moderate heart failure, the time to peak serum concentration of 2.3 ± 1.5 hours (mean ± SD) was increased, and the mean peak serum concentration of 4.8 ± 1.6 mcg/ml was higher than in healthy volunteers. After intravenous administration in these same patients, the mean elimination half-life was 9.7 ± 4.2 hours (range in healthy volunteers of 4.4 to 7.8 hours). In a second study of the oral administration of disopyramide to 7 patients with heart disease, including left ventricular dysfunction, the mean plasma half-life was slightly prolonged to 7.8 ± 1.9 hours (range of 5 to 9.5 hours).

In healthy men, about 50% of a given dose of disopyramide is excreted in the urine as the unchanged drug, about 20% as the mono-N-dealkylated metabolite, and 10% as the other metabolites. The plasma concentration of the major metabolite is approximately one tenth that of disopyramide. Altering the urinary pH in man does not affect the plasma half-life of disopyramide.

In a crossover study in healthy subjects, the bio-availability of disopyramide from Norpace CR capsules was similar to that from the immediate-release capsules. With a single 300-mg oral dose, peak disopyramide plasma concentrations of 3.23 ± 0.75 mcg/ml (mean ± SD) at 2.5 ± 2.3 hours were obtained with two 150-mg immediate-release capsules and 2.22 ± 0.47 mcg/ml at 4.9 ± 1.4 hours with two 150-mg Norpace CR capsules. The elimination half-life of disopyramide was 8.31 ± 1.83 hours with the immediate-release capsules and 11.65 ± 4.72 hours with Norpace CR capsules. The amount of disopyramide and mono-N-dealkylated metabolite excreted in the urine in 48 hours was 128 and 48 mg, respectively, with the immediate-release capsules, and 112 and 33 mg, respectively, with Norpace CR capsules. The differences in the urinary excretion of either constituent were not statistically significant.

Following multiple doses, steady-state plasma levels of between 2 and 4 mcg/ml were attained following either 150 mg every-6-hour dosing with immediate-release capsules or 300 mg every-12-hour dosing with Norpace CR capsules.

Drug Interactions

Effects of other drugs on disopyramide pharmacokinetics: In vitro metabolic studies indicated that disopyramide is metabolized by cytochrome P450 3A4 and that inhibitors of this enzyme may result in elevation of plasma levels of disopyramide. Although specific drug interaction studies have not been done, cases of life-threatening interactions have been reported for disopyramide when given with clarithromycin and erythromycin.

INDICATIONS AND USAGE

Norpace and Norpace CR are indicated for the treatment of documented ventricular arrhythmias, such as sustained ventricular tachycardia, that, in the judgment of the physician, are life-threatening. Because of the proarrhythmic effects of Norpace and Norpace CR, their use with lesser arrhythmias is generally not recommended. Treatment of patients with asymptomatic ventricular premature contractions should be avoided.

Initiation of Norpace or Norpace CR treatment, as with other antiarrhythmic agents used to treat life-threatening arrhythmias, should be carried out in the hospital. Norpace CR should not be used initially if rapid establishment of disopyramide plasma levels is desired.

Antiarrhythmic drugs have not been shown to enhance survival in patients with ventricular arrhythmias.

CONTRAINDICATIONS

Norpace and Norpace CR are contraindicated in the presence of cardiogenic shock, preexisting second-or third-degree AV block (if no pacemaker is present), congenital Q-T prolongation, or known hypersensitivity to the drug.

Warnings

Mortality

In the National Heart, Lung and Blood Institute's Cardiac Arrhythmia Suppression Trial (CAST), a long-term, multi-center, randomized, double-blind study in patients with asymptomatic non-life-threatening ventricular arrhythmias who had had a myocardial infarction more than 6 days but less than 2 years previously, an excessive mortality or non-fatal cardiac arrest rate (7.7%) was seen in patients treated with encainide or flecainide compared with that seen in patients assigned to carefully matched placebo-treated groups (3.0%). The average duration of treatment with encainide or flecainide in this study was 10 months.

The applicability of the CAST results to other populations (e.g., those without recent myocardial infarction) is uncertain. Considering the known proarrhythmic properties of Norpace or Norpace CR and the lack of evidence of improved survival for any antiarrhythmic drug in patients without life-threatening arrhythmias, the use of Norpace or Norpace CR as well as other antiarrhythmic agents should be reserved for patients with life-threatening ventricular arrhythmias.

Negative Inotropic Properties:

Heart Failure/Hypotension

Norpace or Norpace CR may cause or worsen congestive heart failure or produce severe hypotension as a consequence of its negative inotropic properties. Hypotension has been observed primarily in patients with primary cardiomyopathy or inadequately compensated congestive heart failure. Norpace or Norpace CR should not be used in patients with uncompensated or marginally compensated congestive heart failure or hypotension unless the congestive heart failure or hypotension is secondary to cardiac arrhythmia. Patients with a history of heart failure may be treated with Norpace or Norpace CR, but careful attention must be given to the maintenance of cardiac function, including optimal digitalization. If hypotension occurs or congestive heart failure worsens, Norpace or Norpace CR should be discontinued and, if necessary, restarted at a lower dosage only after adequate cardiac compensation has been established.

QRS Widening

Although it is unusual, significant widening (greater than 25%) of the QRS complex may occur during Norpace or Norpace CR administration; in such cases Norpace or Norpace CR should be discontinued.

Q-T Prolongation

As with other Type 1 antiarrhythmic drugs, prolongation of the Q-T interval (corrected) and worsening of the arrhythmia, including ventricular tachycardia and ventricular fibrillation, may occur. Patients who have evidenced prolongation of the Q-T interval in response to quinidine may be at particular risk. As with other Type 1A antiarrhythmics, disopyramide phosphate has been associated with torsade de pointes.

If a Q-T prolongation of greater than 25% is observed and if ectopy continues, the patient should be monitored closely, and consideration given to discontinuing Norpace or Norpace CR.

Hypoglycemia

In rare instances significant lowering of blood-glucose values has been reported during Norpace administration. The physician should be alert to this possibility, especially in patients with congestive heart failure, chronic malnutrition, hepatic, renal or other diseases, or drugs (e.g., beta-adrenoceptor blockers, alcohol) which could compromise preservation of the normal glucoregulatory mechanisms in the absence of food. In these patients the blood-glucose levels should be carefully followed.

Concomitant Antiarrhythmic Therapy

The concomitant use of Norpace or Norpace CR with other Type 1A antiarrhythmic agents (such as quinidine or procainamide), Type 1C antiarrhythmics (such as encainide, flecainide or propafenone), and/or propranolol should be reserved for patients with life-threatening arrhythmias who are demonstrably unresponsive to single-agent antiarrhythmic therapy. Such use may produce serious negative inotropic effects, or may excessively prolong conduction. This should be considered particularly in patients with any degree of cardiac decompensation or those with a prior history thereof. Patients receiving more than one antiarrhythmic drug must be carefully monitored.

Heart Block

If first-degree heart block develops in a patient receiving Norpace or Norpace CR, the dosage should be reduced. If the block persists despite reduction of dosage, continuation of the drug must depend upon weighing the benefit being obtained against the risk of higher degrees of heart block. Development of second- or third-degree AV block or unifascicular, bifascicular, or trifascicular block requires discontinuation of Norpace or Norpace CR therapy, unless the ventricular rate is adequately controlled by a temporary or implanted ventricular pacemaker.

Anticholinergic Activity

Because of its anticholinergic activity, disopyramide phosphate should not be used in patients with glaucoma, myasthenia gravis, or urinary retention unless adequate overriding measures are taken; these consist of the topical application of potent miotics (e.g., pilocarpine) for patients with glaucoma, and catheter drainage or operative relief for patients with urinary retention. Urinary retention may occur in patients of either sex as a consequence of Norpace or Norpace CR administration, but males with benign prostatic hypertrophy are at particular risk. In patients with a family history of glaucoma, intraocular pressure should be measured before initiating Norpace or Norpace CR therapy. Disopyramide phosphate should be used with special care in patients with myasthenia gravis since its anticholinergic properties could precipitate a myasthenic crisis in such patients.

PRECAUTIONS

General

Atrial Tachyarrhythmias

Patients with atrial flutter or fibrillation should be digitalized prior to Norpace or Norpace CR administration to ensure that drug-induced enhancement of AV conduction does not result in an increase of ventricular rate beyond physiologically acceptable limits.

Conduction Abnormalities

Care should be taken when prescribing Norpace or Norpace CR for patients with sick sinus syndrome (bradycardia-tachycardia syndrome), Wolff-Parkinson-White syndrome (WPW), or bundle branch block. The effect of disopyramide phosphate in these conditions is uncertain at present.

Cardiomyopathy

Patients with myocarditis or other cardiomyopathy may develop significant hypotension in response to the usual dosage of disopyramide phosphate, probably due to cardiodepressant mechanisms. Therefore, a loading dose of Norpace should not be given to such patients, and initial dosage and subsequent dosage adjustments should be made under close supervision (see Dosage and Administration).

Renal Impairment

More than 50% of disopyramide is excreted in the urine unchanged. Therefore Norpace dosage should be reduced in patients with impaired renal function (see Dosage and Administration). The electrocardiogram should be carefully monitored for prolongation of PR interval, evidence of QRS widening, or other signs of overdosage (see Overdosage).

Norpace CR is not recommended for patients with severe renal insufficiency (creatinine clearance 40 ml/min or less).

Hepatic Impairment

Hepatic impairment also causes an increase in the plasma half-life of disopyramide. Dosage should be reduced for patients with such impairment. The electrocardiogram should be carefully monitored for signs of overdosage (see Overdosage).

Patients with cardiac dysfunction have a higher potential for hepatic impairment; this should be considered when administering Norpace or Norpace CR.

Potassium Imbalance

Antiarrhythmic drugs may be ineffective in patients with hypokalemia, and their toxic effects may be enhanced in patients with hyperkalemia. Therefore, potassium abnormalities should be corrected before starting Norpace or Norpace CR therapy.

Drug Interactions

If phenytoin or other hepatic enzyme inducers are taken concurrently with Norpace or Norpace CR, lower plasma levels of disopyramide may occur. Monitoring of disopyramide plasma levels is recommended in such concurrent use to avoid ineffective therapy. Other antiarrhythmic drugs (e.g., quinidine, procainamide, lidocaine, propranolol) have occasionally been used concurrently with Norpace. Excessive widening of the QRS complex and/or prolongation of the Q-T interval may occur in these situations (see Warnings). In healthy subjects, no significant drug-drug interaction was observed when Norpace was coadministered with either propranolol or diazepam. Concomitant administration of Norpace and quinidine resulted in slight increases in plasma disopyramide levels and slight decreases in plasma quinidine levels. Norpace does not increase serum digoxin levels.

Until data on possible interactions between verapamil and disopyramide phosphate are obtained, disopyramide should not be administered within 48 hours before or 24 hours after verapamil administration.

Although potent inhibitors of cytochrome P450 3A4 (e.g., ketoconazole) have not been studied clinically, in vitro studies have shown that erythromycin and oleandomycin inhibit the metabolism of disopyramide. Cases of life-threatening interactions have been reported for disopyramide when given with clarithromycin and erythromycin indicating that coadministration of disopyramide with inhibitors of cytochrome 3A4 could result in potentially fatal interaction.

Carcinogenesis, Mutagenesis, Impairment of Fertility

Eighteen months of Norpace administration to rats, at oral doses up to 400 mg/kg/day (about 30 times the usual daily human dose of 600 mg/day, assuming a patient weight of at least 50 kg), revealed no evidence of carcinogenic potential. An evaluation of mutagenic potential by Ames test was negative. Norpace, at doses up to 250 mg/kg/day, did not adversely affect fertility of rats.

Pregnancy

Teratogenic Effects

Norpace was associated with decreased numbers of implantation sites and decreased growth and survival of pups when administered to pregnant rats at 250 mg/kg/day (20 or more times the usual daily human dose of 12 mg/kg, assuming a patient weight of at least 50 kg), a level at which weight gain and food consumption of dams were also reduced. Increased resorption rates were reported in rabbits at 60 mg/kg/day (5 or more times the usual daily human dose). Effects on implantation, pup growth, and survival were not evaluated in rabbits. There are no adequate and well-controlled studies in pregnant women. Norpace or Norpace CR should be used during pregnancy only if the potential benefit justifies the potential risk to the fetus.

Nonteratogenic Effects: Norpace has been reported to stimulate contractions of the pregnant uterus. Disopyramide has been found in human fetal blood.

Labor and Delivery

It is not known whether the use of Norpace or Norpace CR during labor or delivery has immediate or delayed adverse effects on the fetus, or whether it prolongs the duration of labor or increases the need for forceps delivery or other obstetric intervention.

Nursing Mothers

Studies in rats have shown that the concentration of disopyramide and its metabolites is between one and three times greater in milk than it is in plasma. Following oral administration, disopyramide has been detected in human milk at a concentration not exceeding that in plasma. Because of the potential for serious adverse reactions in nursing infants from Norpace or Norpace CR, a decision should be made whether to discontinue nursing or to discontinue the drug, taking into account the importance of the drug to the mother.

Pediatric Use

Safety and effectiveness in pediatric patients have not been established (see Dosage and Administration).

Geriatric Use

Clinical studies of Norpace/Norpace CR did not include sufficient numbers of subjects aged 65 and over to determine whether they respond differently from younger subjects. Other reported clinical experience has not identified differences in responses between the elderly and younger patients. In general, dose selection for an elderly patient should be cautious, usually starting at the low end of the dosing range, reflecting the greater frequency of decreased hepatic, renal, or cardiac function, and of concomitant disease or other drug therapy.

Because of its anticholinergic activity, disopyramide phosphate should not be used in patients with glaucoma, urinary retention, or benign prostatic hypertrophy (medical conditions commonly associated with the elderly) unless adequate overriding measures are taken (see Warnings: Anticholinergic Activity). In the event of increased anticholinergic side effects, plasma levels of disopyramide should be monitored and the dose of the drug adjusted accordingly. A reduction of the dose by one third, from the recommended 600 mg/day to 400 mg/day, would be reasonable, without changing the dosing interval.

This drug is known to be substantially excreted by the kidney, and the risk of toxic reactions to this drug may be greater in patients with impaired renal function. Because elderly patients are more likely to have decreased renal function, care should be taken in dose selection, and it may be useful to monitor renal function (see Precautions: Renal Impairment and Dosage and Administration).

ADVERSE REACTIONS

The adverse reactions which were reported in Norpace clinical trials encompass observations in 1,500 patients, including 90 patients studied for at least 4 years. The most serious adverse reactions are hypotension and congestive heart failure. The most common adverse reactions, which are dose dependent, are associated with the anticholinergic properties of the drug. These may be transitory, but may be persistent or can be severe. Urinary retention is the most serious anticholinergic effect.

The following reactions were reported in 10% to 40% of patients:

Anticholinergic: dry mouth (32%), urinary hesitancy (14%), constipation (11%)

The following reactions were reported in 3% to 9% of patients:

Anticholinergic: blurred vision, dry nose/eyes/throat

Genitourinary: urinary retention, urinary frequency and urgency

Gastrointestinal: nausea, pain/bloating/gas

General: dizziness, general fatigue/muscle weakness, headache, malaise, aches/pains

The following reactions were reported in 1% to 3% of patients:

Genitourinary: impotence

Cardiovascular: hypotension with or without congestive heart failure, increased congestive heart failure (see Warnings), cardiac conduction disturbances (see Warnings), edema/weight gain, shortness of breath, syncope, chest pain

Gastrointestinal: anorexia, diarrhea, vomiting

Dermatologic: generalized rash/dermatoses, itching

Central nervous system: nervousness

Other: hypokalemia, elevated cholesterol/triglycerides

The following reactions were reported in less than 1%:

Depression, insomnia, dysuria, numbness/tingling, elevated liver enzymes, AV block, elevated BUN, elevated creatinine, decreased hemoglobin/hematocrit

Hypoglycemia has been reported in association with Norpace administration (see Warnings).

Infrequent occurrences of reversible cholestatic jaundice, fever, and respiratory difficulty have been reported in association with disopyramide therapy, as have rare instances of thrombocytopenia, reversible agranulocytosis, and gynecomastia. Some cases of LE (lupus erythematosus) symptoms have been reported; most cases occurred in patients who had been switched to disopyramide from procainamide following the development of LE symptoms. Rarely, acute psychosis has been reported following Norpace therapy, with prompt return to normal mental status when therapy was stopped. The physician should be aware of these possible reactions and should discontinue Norpace or Norpace CR therapy promptly if they occur.

OVERDOSAGE

Symptoms

Deliberate or accidental overdosage of oral disopyramide may be followed by apnea, loss of consciousness, cardiac arrhythmias, and loss of spontaneous respiration. Death has occurred following overdosage.

Toxic plasma levels of disopyramide produce excessive widening of the QRS complex and Q-T interval, worsening of congestive heart failure, hypotension, varying kinds and degrees of conduction disturbance, bradycardia, and finally asystole. Obvious anticholinergic effects are also observed.

The approximate oral LD50 of disopyramide phosphate is 580 and 700 mg/kg for rats and mice, respectively.

Treatment

Experience indicates that prompt and vigorous treatment of overdosage is necessary, even in the absence of symptoms. Such treatment may be life-saving. No specific antidote for disopyramide phosphate has been identified. Treatment should be symptomatic and may include induction of emesis or gastric lavage, administration of a cathartic followed by activated charcoal by mouth or stomach tube, intravenous administration of isoproterenol and dopamine, insertion of an intra-aortic balloon for counterpulsation, and mechanically assisted ventilation. Hemodialysis or, preferably, hemoperfusion with charcoal may be employed to lower serum concentration of the drug.

The electrocardiogram should be monitored, and supportive therapy with cardiac glycosides and diuretics should be given as required.

If progressive AV block should develop, endocardial pacing should be implemented. In case of any impaired renal function, measures to increase the glomerular filtration rate may reduce the toxicity (disopyramide is excreted primarily by the kidney).

The anticholinergic effects can be reversed with neostigmine at the discretion of the physician.

Altering the urinary pH in humans does not affect the plasma half-life or the amount of disopyramide excreted in the urine.

DOSAGE AND ADMINISTRATION

The dosage of Norpace or Norpace CR must be individualized for each patient on the basis of response and tolerance. The usual adult dosage of Norpace or Norpace CR is 400 to 800 mg per day given in divided doses. The recommended dosage for most adults is 600 mg/day given in divided doses (either 150 mg every 6 hours for immediate-release Norpace or 300 mg every 12 hours for Norpace CR). For patients whose body weight is less than 110 pounds (50 kg), the recommended dosage is 400 mg/day given in divided doses (either 100 mg every 6 hours for immediate-release Norpace or 200 mg every 12 hours for Norpace CR). In the event of increased anticholinergic side effects, plasma levels of disopyramide should be monitored and the dose of the drug adjusted accordingly. A reduction of the dose by one third, from the recommended 600 mg/day to 400 mg/day, would be reasonable, without changing the dosing interval.

For patients with cardiomyopathy or possible cardiac decompensation, a loading dose, as discussed below, should not be given, and initial dosage should be limited to 100 mg of immediate-release Norpace every 6 to 8 hours. Subsequent dosage adjustments should be made gradually, with close monitoring for the possible development of hypotension and/or congestive heart failure (see Warnings).

For patients with moderate renal insufficiency (creatinine clearance greater than 40 ml/min) or hepatic insufficiency, the recommended dosage is 400 mg/day given in divided doses (either 100 mg every 6 hours for immediate-release Norpace or 200 mg every 12 hours for Norpace CR).

For patients with severe renal insufficiency (Ccr 40 ml/min or less), the recommended dosage regimen of immediate-release Norpace is 100 mg at intervals shown in the table below, with or without an initial loading dose of 150 mg.

IMMEDIATE-RELEASE NORPACE DOSAGE INTERVAL FOR PATIENTS WITH RENAL INSUFFICIENCY
Creatinine Clearance (ml/min) | 40–30 | 30–15 | Less than 15
Approximate Maintenance-dosing interval | q 8 hr | q 12 hr | Q 24 hr

The above dosing schedules are for Norpace immediate-release capsules; Norpace CR is not recommended for patients with severe renal insufficiency.

For patients in whom rapid control of ventricular arrhythmia is essential, an initial loading dose of 300 mg of immediate-release Norpace (200 mg for patients whose body weight is less than 110 pounds) is recommended, followed by the appropriate maintenance dosage. Therapeutic effects are usually attained 30 minutes to 3 hours after administration of a 300-mg loading dose. If there is no response or evidence of toxicity within 6 hours of the loading dose, 200 mg of immediate-release Norpace every 6 hours may be prescribed instead of the usual 150 mg. If there is no response to this dosage within 48 hours, either Norpace should then be discontinued or the physician should consider hospitalizing the patient for careful monitoring while subsequent immediate-release Norpace doses of 250 mg or 300 mg every 6 hours are given. A limited number of patients with severe refractory ventricular tachycardia have tolerated daily doses of Norpace up to 1600 mg per day (400 mg every 6 hours), resulting in disopyramide plasma levels up to 9 mcg/ml. If such treatment is warranted, it is essential that patients be hospitalized for close evaluation and continuous monitoring.

Norpace CR should not be used initially if rapid establishment of disopyramide plasma levels is desired.

Transferring to Norpace or Norpace CR.

The following dosage schedule based on theoretical considerations rather than experimental data is suggested for transferring patients with normal renal function from either quinidine sulfate or procainamide therapy (Type 1 antiarrhythmic agents) to Norpace or Norpace CR therapy:

Norpace or Norpace CR should be started using the regular maintenance schedule without a loading dose 6 to 12 hours after the last dose of quinidine sulfate or 3 to 6 hours after the last dose of procainamide.

In patients in whom withdrawal of quinidine sulfate or procainamide is likely to produce life-threatening arrhythmias, the physician should consider hospitalization of the patient. When transferring a patient from immediate-release Norpace to Norpace CR, the maintenance schedule of Norpace CR may be started 6 hours after the last dose of immediate-release Norpace.

Pediatric Dosage

Controlled clinical studies have not been conducted in pediatric patients; however, the following suggested dosage table is based on published clinical experience.

Total daily dosage should be divided and equal doses administered orally every 6 hours or at intervals according to individual patient needs. Disopyramide plasma levels and therapeutic response must be monitored closely. Patients should be hospitalized during the initial treatment period, and dose titration should start at the lower end of the ranges provided below.

SUGGESTED TOTAL DAILY DOSAGE [Dosage is expressed in milligrams of disopyramide base. Since Norpace (disopyramide phosphate) 100-mg capsules contain 100 mg of disopyramide base, the pharmacist can readily prepare a 1-mg/ml to 10-mg/ml liquid suspension by adding the entire contents of Norpace capsules to cherry syrup. (Prepare cherry syrup as follows: cherry juice, 475 ml; sucrose 800 g; alcohol, 20 ml; purified water, a sufficient quantity to make 1000 ml.) The resulting suspension, when refrigerated, is stable for one month and should be thoroughly shaken before the measurement of each dose. The suspension should be dispensed in an amber glass bottle with a child-resistant closure.]
Age (years) | Disopyramide (mg/kg body weight/day)
Under 1 | 10 to 30
1 to 4 | 10 to 20
4 to 12 | 10 to 15
12 to 18 | 6 to 15

Norpace CR capsules should not be used to prepare the above suspension.

HOW SUPPLIED

Norpace (disopyramide phosphate) is supplied in hard gelatin capsules containing either 100 mg or 150 mg of disopyramide base, present as the phosphate.

Norpace 100-mg capsules are white and orange, with markings SEARLE, 2752, NORPACE, and 100 MG.

NDC Number | Size
0025-2752-31 | bottle of 100

Norpace 150-mg capsules are brown and orange, with markings SEARLE, 2762, NORPACE, and 150 MG.

NDC Number | Size
0025-2762-31 | bottle of 100

Norpace CR (disopyramide phosphate) Controlled-Release is supplied as specially prepared controlled-release beads in hard gelatin capsules containing either 100 mg or 150 mg of disopyramide base, present as the phosphate.

Norpace CR 100-mg capsules are white and light green, with markings SEARLE, 2732, NORPACE CR, and 100 mg.

NDC Number | Size
0025-2732-31 | bottle of 100

Norpace CR 150-mg capsules are brown and light green, with markings SEARLE, 2742, NORPACE CR, and 150 mg.

NDC Number | Size
0025-2742-31 | bottle of 100

STORAGE AND HANDLING

Store at 25°C (77°F); excursions permitted to 15–30°C (59–86°F). [See USP Controlled Room Temperature.]

Rx only

LAB-0066-8.0
Revised August 2023

PRINCIPAL DISPLAY PANEL - 100 mg Capsule Bottle Label

NDC 0025-2752-31

Pfizer

Norpace®
disopyramide phosphate
capsules USP

100 mg*

100 Capsules
Rx only

PRINCIPAL DISPLAY PANEL - 150 mg Capsule Bottle Label

NDC 0025-2762-31

Pfizer

Norpace®
disopyramide phosphate
capsules USP

150 mg*

100 Capsules
Rx only

PRINCIPAL DISPLAY PANEL - 100 mg Capsule Bottle Label - NDC 0025-2732-31

NDC 0025-2732-31

Pfizer

Norpace® CR
disopyramide phosphate
extended-release
capsules USP

100 mg*

100 Capsules
Rx only

PRINCIPAL DISPLAY PANEL - 150 mg Capsule Bottle Label - NDC 0025-2742-31

NDC 0025-2742-31

Pfizer

Norpace® CR
disopyramide phosphate
extended-release
capsules USP

150 mg*

100 Capsules
Rx only